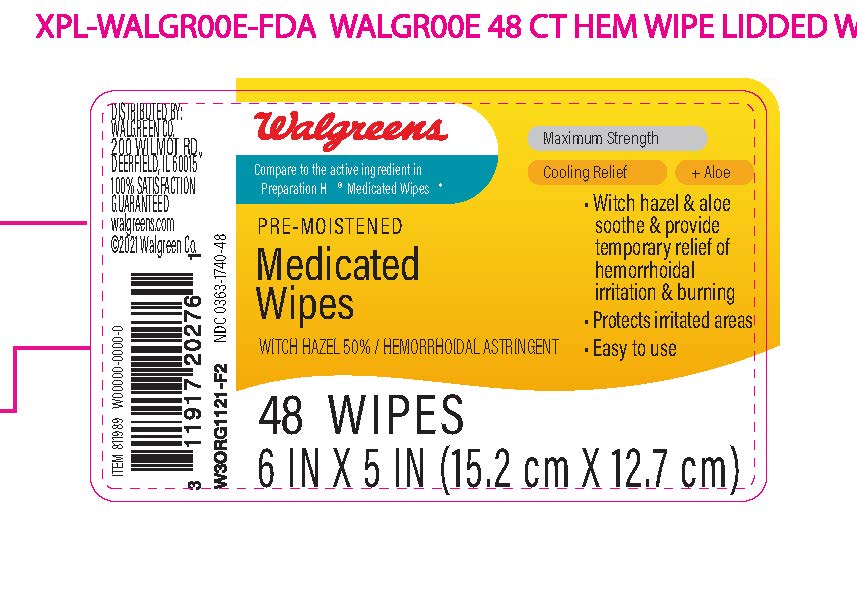 DRUG LABEL: Pre-moistened Medicated Wipes, Pre-moistened Medicated Wipes Witch Hazel 50%/Hemorrhoidal Astringent, Walgreens Pre-moistened Medicated Wipes, Walgreens Pre-moistened Medicated Wipes Witch Hazel 50%/Hemorrhoidal Astringent
NDC: 0363-1740 | Form: CLOTH
Manufacturer: Walgreens Company
Category: otc | Type: HUMAN OTC DRUG LABEL
Date: 20250115

ACTIVE INGREDIENTS: WITCH HAZEL 50 mg/100 mg
INACTIVE INGREDIENTS: WATER; SODIUM CITRATE; ANHYDROUS CITRIC ACID; GLYCERIN; PHENOXYETHANOL; POTASSIUM SORBATE; ALOE VERA LEAF

Drug Facts

Active Ingredient

Witch Hazel, 50%

Purpose

Hemorrhoidal Astringent

Uses

Temporarily relieves these external symptoms associated with hemorrhoids:

- itching
- burning
- irritation

Warnings

For external use only.

When using this product

- do not exceed the recommended daily dosage unless directed by a doctor.
- do not insert into rectum or vagina using fingers or mechanical device.

Stop use and ask a doctor if

- rectal bleeding occurs
- condition worsens or does not improve within 7 days.

Keep out of reach of children.

If swallowed, get medical help or contact a Poison Control Center right away at 1-800-222-1222.

Directions

As hemorrhoidal treatment for adults:

- when practical, cleanse the affected area with mild soap and warm water and rinse thoroughly.
- gently dry by patting or blotting with toilet tissue or soft cloth before applying.
- gently apply to the affected area by patting and then discard.
- can be used up to six times daily or after each bowel movement.

Children under 12 years of age

- consult a doctor.

Other Information

Store at controlled room temperature: 15º-30ºC (59º-86ºF)

Inactive Ingredients

aloe barbadensis leaf extract, citric acid, glycerin, phenoxyethanol, potassium sorbate, sodium citrate, water

Principal Display Panel

NDC 0363-1740-48

Walgreens

Compare to the active ingredient in Preparation H® Medicated Wipes*

Pre-Moistened Medicated Wipes

WITCH HAZEL 50%/HEMORRHOIDAL ASTRINGENT

Maximum Strength

Cooling Relef

+Aloe

Witch hazel & aloe soothe & provide temporary relief of hemorrhoidal irritation & burning
Protects irritated areas
Easy to Use

48 WIPES

6 IN X 5 IN (15.2 cm X 12.7 cm)